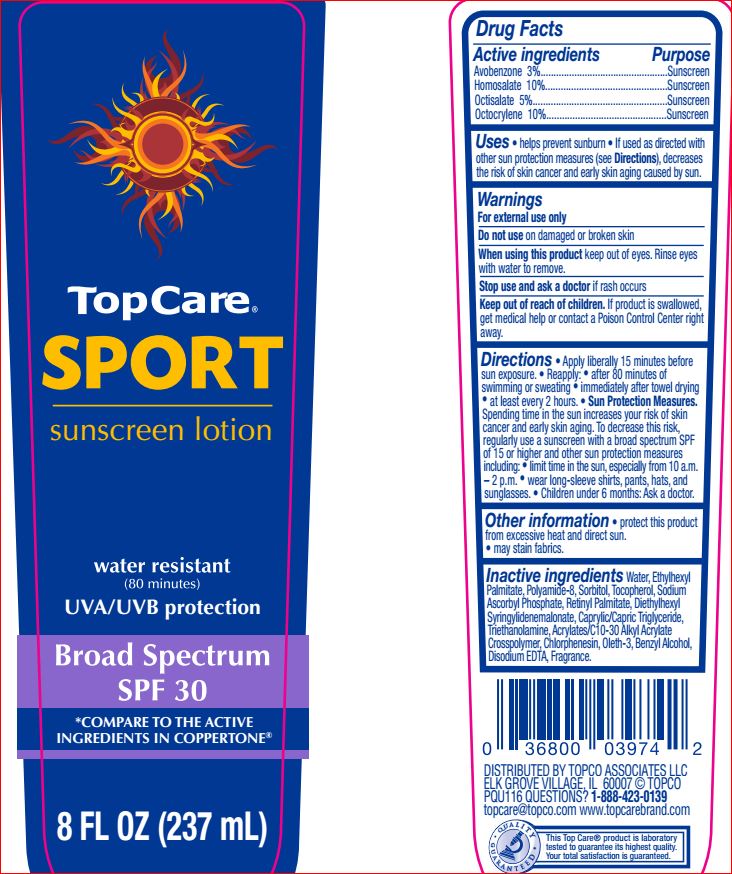 DRUG LABEL: Sport Sunscreen SPF 30
NDC: 36800-712 | Form: LOTION
Manufacturer: TopCare
Category: otc | Type: HUMAN OTC DRUG LABEL
Date: 20180629

ACTIVE INGREDIENTS: Avobenzone 3 g/100 mL; Homosalate 10 g/100 mL; Octisalate 5 g/100 mL; Octocrylene 10 g/100 mL
INACTIVE INGREDIENTS: BENZYL ALCOHOL; MEDIUM-CHAIN TRIGLYCERIDES; CHLORPHENESIN; DIETHYLHEXYL SYRINGYLIDENEMALONATE; EDETATE DISODIUM ANHYDROUS; ETHYLHEXYL PALMITATE; OLETH-3; VITAMIN A PALMITATE; SODIUM ASCORBYL PHOSPHATE; SORBITOL; TOCOPHEROL; TROLAMINE; WATER

Drug Facts

Active ingredients Purpose
Avobenzone 3%.................................................Sunscreen
Homosalate 10%...............................................Sunscreen
Octisalate 5%....................................................Sunscreen
Octocrylene 10%........................... ...................Sunscreen

INDICATIONS AND USAGE

Uses • helps prevent sunburn • If used as directed with
other sun protection measures (see Directions), decreases
the risk of skin cancer and early skin aging caused by sun

Warnings
For external use only
Do not use on damaged or broken skin
When using this product keep out of eyes. Rinse eyes
with water to remove.
Stop use and ask a doctor if rash occurs
Keep out of reach of children. If product is swallowed,
get medical help or contact a Poison Control Center right
away.

DOSAGE AND ADMINISTRATION

Directions • Apply liberally 15 minutes before
sun exposure. • Reapply: • after 80 minutes of
swimming or sweating • immediately after towel drying
• at least every 2 hours. • Sun Protection Measures.
Spending time in the sun increases your risk of skin
cancer and early skin aging. To decrease this risk,
regularly use a sunscreen with a broad spectrum SPF
of 15 or higher and other sun protection measures
including: • limit time in the sun, especially from 10 a.m.
– 2 p.m. • wear long-sleeve shirts, pants, hats, and
sunglasses. • Children under 6 months: Ask a doctor

Other information • protect this product
from excessive heat and direct sun.
• may stain fabrics.

Inactive ingredients

Water, Ethylhexyl
Palmitate, Polyamide-8, Sorbitol, Tocopherol, Sodium
Ascorbyl Phosphate, Retinyl Palmitate, Diethylhexyl
Syringylidenemalonate, Caprylic/Capric Triglyceride,
Triethanolamine, Acrylates/C10-30 Alkyl Acrylate
Crosspolymer, Chlorphenesin, Oleth-3, Benzyl Alcohol,
Disodium EDTA, Fragrance